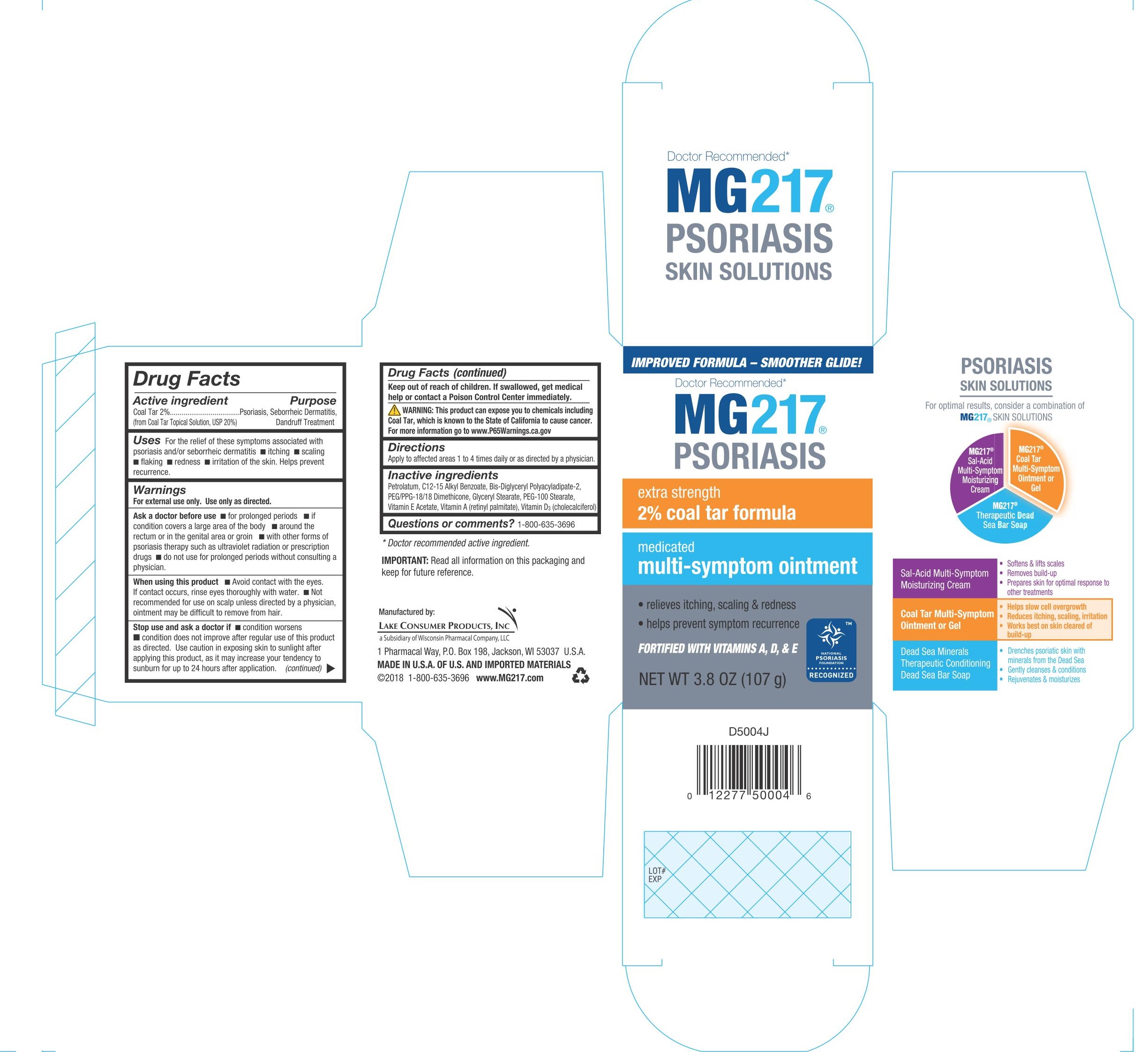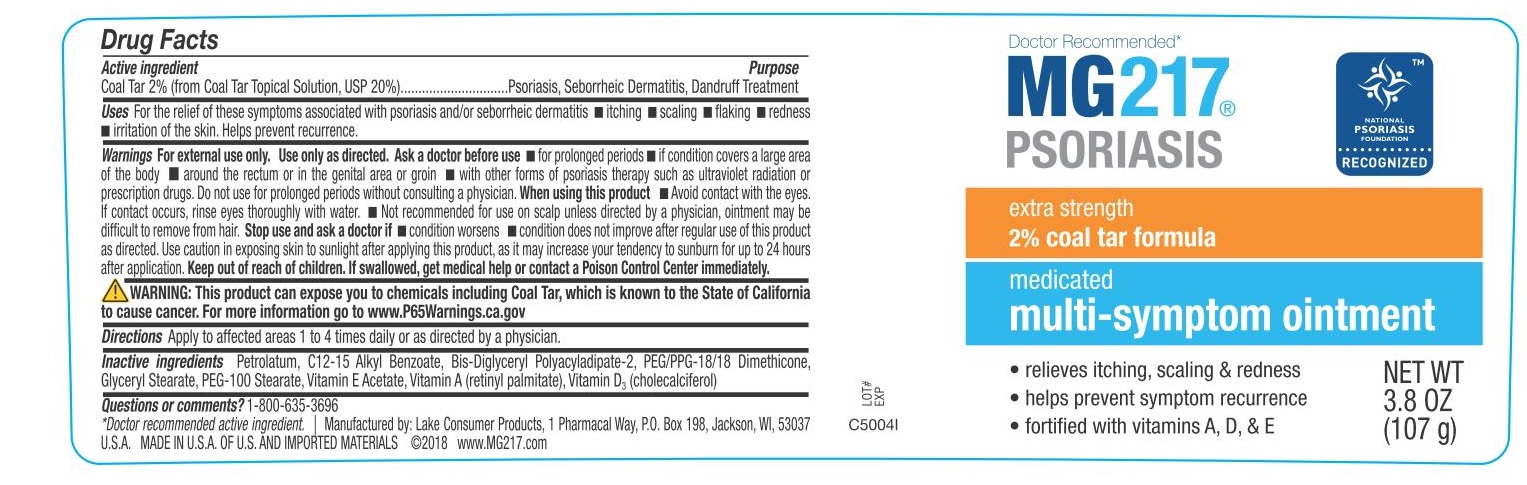 DRUG LABEL: MG217 Psoriasis
NDC: 68093-7233 | Form: OINTMENT
Manufacturer: Wisconsin Pharmacal Company
Category: otc | Type: HUMAN OTC DRUG LABEL
Date: 20181210

ACTIVE INGREDIENTS: COAL TAR 0.03 g/1 g
INACTIVE INGREDIENTS: BIS-DIGLYCERYL POLYACYLADIPATE-2; CHOLECALCIFEROL; PETROLATUM; .ALPHA.-TOCOPHEROL, D-; GLYCERYL MONOSTEARATE; ALKYL (C12-15) BENZOATE; PEG/PPG-18/18 DIMETHICONE; PEG-100 STEARATE; VITAMIN A PALMITATE

Active ingredient

Coal Tar 2% (from Coal Tar Topical Solution, USP 20%)

Purpose

Psoriasis, Seborrheic Dermatitis, Dandruff Treatment

INDICATIONS AND USAGE

Uses For the relief of these symptoms associated with psoriasis and/or seborrheic dermatitis ■ itching ■ scaling
■ ﬂaking ■ redness ■ irritation of the skin. Helps prevent recurrence.

Warnings
For external use only. Use only as directed.

Ask a doctor before use ■ for prolonged periods ■ if condition covers a large area of the body ■ around the rectum or in the genital area or groin ■ with other forms of psoriasis therapy such as ultraviolet radiation or prescription drugs ■ do not use for prolonged periods without consulting a physician.

When using this product ■ Avoid contact with the eyes. If contact occurs, rinse eyes thoroughly with water. ■ Not recommended for use on scalp unless directed by a physician, ointment may be difﬁcult to remove from hair.

Stop use and ask a doctor if ■ condition worsens ■ condition does not improve after regular use of this product as directed. Use caution in exposing skin to sunlight after applying this product, as it may increase your tendency to sunburn for up to 24 hours after application.

Keep out of reach of children. If swallowed, get medical help or contact a Poison Control Center immediately.

OTHER SAFETY INFORMATION

WARNING: This product can expose you to chemicals including Coal Tar, which is known to the State of California to cause cancer. For more information go to www.P65Warnings.ca.gov

Directions
Apply to affected areas 1 to 4 times daily or as directed by a physician.

Inactive ingredients
Petrolatum, C12-15 Alkyl Benzoate, Bis-Diglyceryl Polyacyladipate-2, PEG/PPG-18/18 Dimethicone, Glyceryl Stearate, PEG-100 Stearate, Vitamin E Acetate, Vitamin A (retinyl palmitate), Vitamin D 3 (cholecalciferol)

Questions or comments? 1-800-635-3696